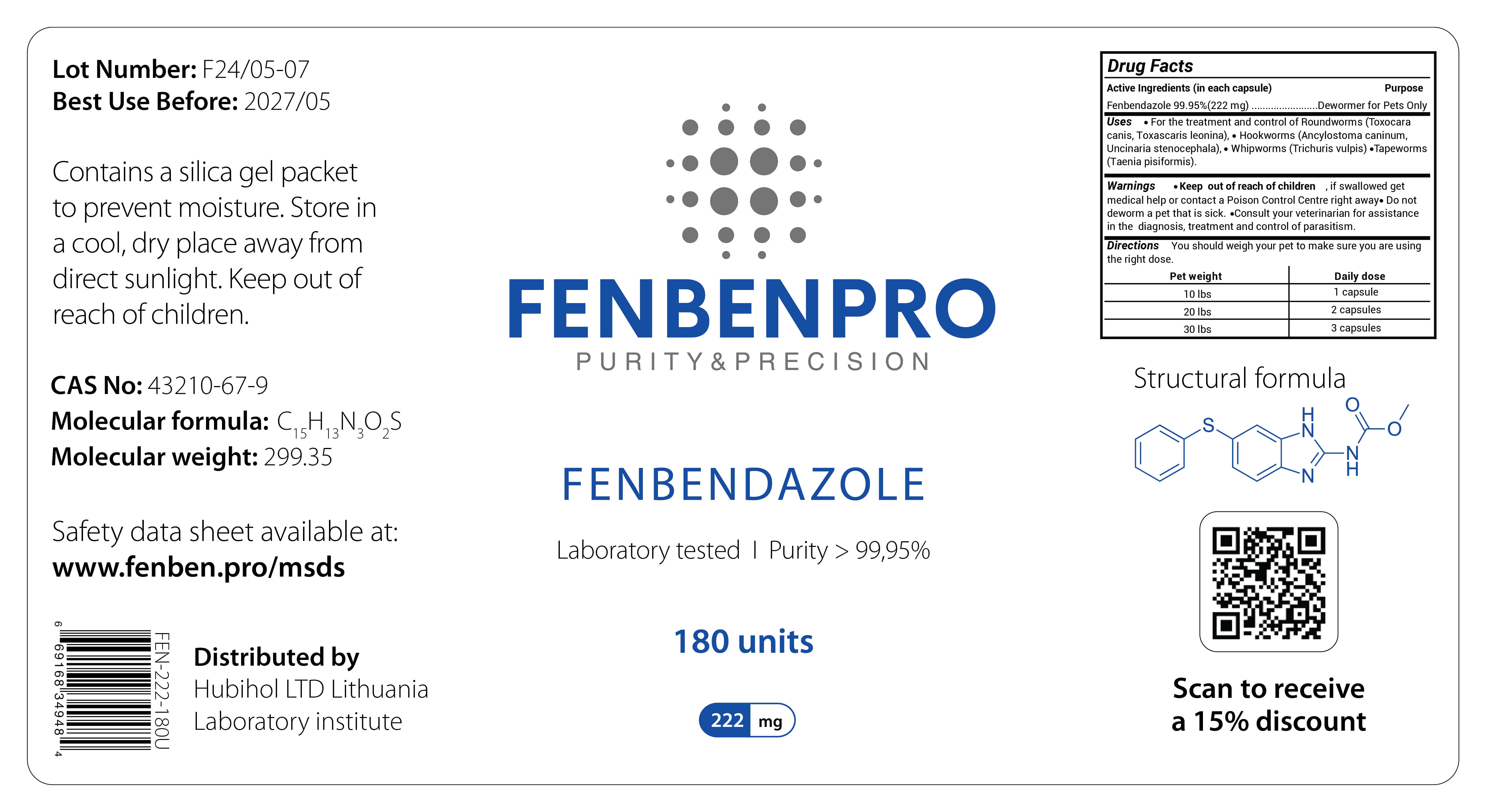 DRUG LABEL: FENBENPRO PURITY and PRECISION FENBENDAZOLE
NDC: 86217-0005 | Form: CAPSULE
Manufacturer: HUBIHOL, UAB
Category: animal | Type: OTC ANIMAL DRUG LABEL
Date: 20250201

ACTIVE INGREDIENTS: FENBENDAZOLE 222 mg/180 U

FENBENPRO PURITY and PRECISION FENBENDAZOLE

Active Ingredients

Active Ingredients (in each capsule)
Fenbendazole 99.95% (222 mg).

Package Labeling

FENBENPRO PURITY and PRECISION FENBENDAZOLE

Lot Number: F24/05-07 Best Use Before: 2027/05
Contains a silica gel packet to prevent moisture. Store in a cool, dry place away from
direct sunlight. Keep out of
reach of children.
CAS No: 43210-67-9
FENBENPRO
PURITY & PRECISION
Molecular formula: C, H,,N,O,S
15' '13
3
Molecular weight: 299.35
Safety data sheet available at: www.fenben.pro/msds
6
69168 34948
4
FEN-222-180U
Distributed by
Hubihol LTD Lithuania Laboratory institute
FENBENDAZOLE
Laboratory tested | Purity > 99,95%
180 units
222 mg
Drug Facts
Active Ingredients (in each capsule)
Fenbendazole 99.95% (222 mg).
•
Purpose
.....Dewormer for Pets Only
Uses • For the treatment and control of Roundworms (Toxocara canis, Toxascaris leonina), Hookworms (Ancylostoma caninum, Uncinaria stenocephala), Whipworms (Trichuris vulpis) ⚫Tapeworms (Taenia pisiformis).
Warnings
•
Keep out of reach of children if swallowed get medical help or contact a Poison Control Centre right away. Do not deworm a pet that is sick. Consult your veterinarian for assistance in the diagnosis, treatment and control of parasitism. Directions You should weigh your pet to make sure you are using the right dose.
Pet weight
10 lbs
20 lbs
30 lbs
Daily dose
1 capsule
2 capsules
3 capsules